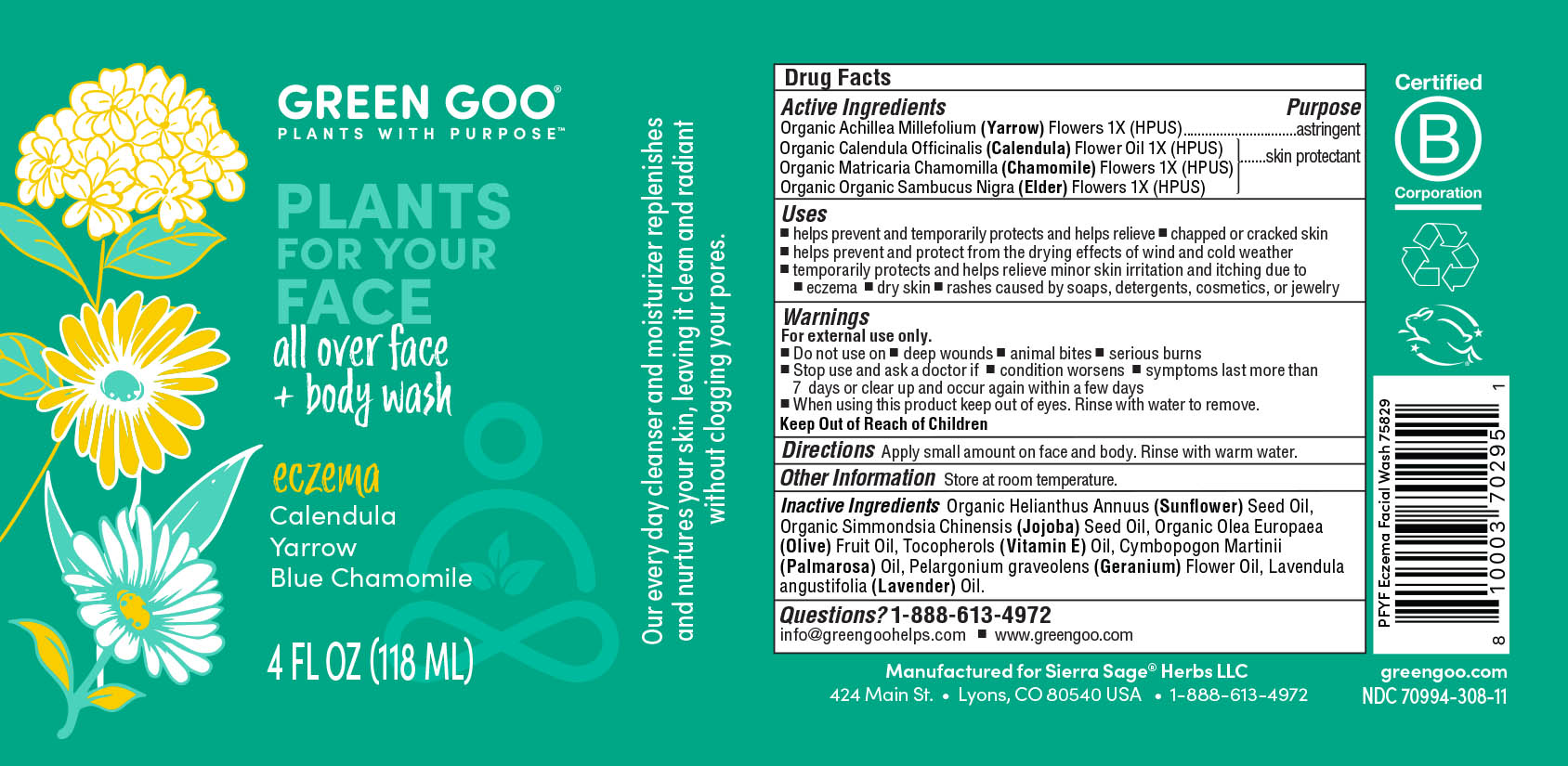 DRUG LABEL: Eczema Face and Body Wash
NDC: 70994-307 | Form: OIL
Manufacturer: Spry Life LLC
Category: homeopathic | Type: HUMAN OTC DRUG LABEL
Date: 20251215

ACTIVE INGREDIENTS: CALENDULA OFFICINALIS FLOWER 1 [hp_X]/100 mL; SAMBUCUS NIGRA FLOWER 1 [hp_X]/100 mL; MATRICARIA CHAMOMILLA FLOWERING TOP 1 [hp_X]/100 mL; ACHILLEA MILLEFOLIUM FLOWER 1 [hp_X]/100 mL
INACTIVE INGREDIENTS: OLIVE OIL; PALMAROSA OIL; PELARGONIUM GRAVEOLENS FLOWER OIL; JOJOBA OIL; LAVENDER OIL; SUNFLOWER OIL; ALPHA-TOCOPHEROL

Eczema Face and Body Wash

PURPOSE

Astringent

Skin Protectant

Active Ingredients

Organic Achillea Millefolium (Yarrow) Flowers 1X (HPUS)

Organic Calendula Officinalis (Calendula) Flower Oil 1X (HPUS)

Organic Matricaria Chamomilla (Chamomile) Flowers 1X (HPUS)

Organic Organic Sambucus Nigra (Elder) Flowers 1X (HPUS)

Indications & Usage

■ helps prevent and temporarily protects and helps relieve ■ chapped or cracked skin

■ helps prevent and protect from the drying effects of wind and cold weather

■ temporarily protects and helps relieve minor skin irritation and itching due to

■ rashes ■ dry skin ■ rashes caused by soaps, detergents, cosmetics, or jewelry

Warnings

For external use only.

■ Do not use on ■ deep wounds ■ animal bites ■ serious burns

■ Stop use and ask a doctor if ■ condition worsens ■ symptoms last more than

7 days or clear up and occur again within a few days

■ When using this product keep out of eyes. Rinse with water to remove.

Keep out of Reach of Children

Dosage & Administration

Apply small amount and rinse with warm water.

Storage

Keep at room temperature.

Inactive Ingredients

Organic Helianthus Annuus (Sunflower) Seed Oil, Organic Simmondsia Chinensis (Jojoba) Seed Oil, Organic Olea Europaea

(Olive) Fruit Oil, Tocopherols (Vitamin E) Oil, Cymbopogon Martinii (Palmarosa) Oil, Pelargonium graveolens (Geranium) Flower Oil, Lavendula angustifolia (Lavender) Oil.

Questions

1-888-613-4972

info@greengoohelps.com ■ www.greengoo.com